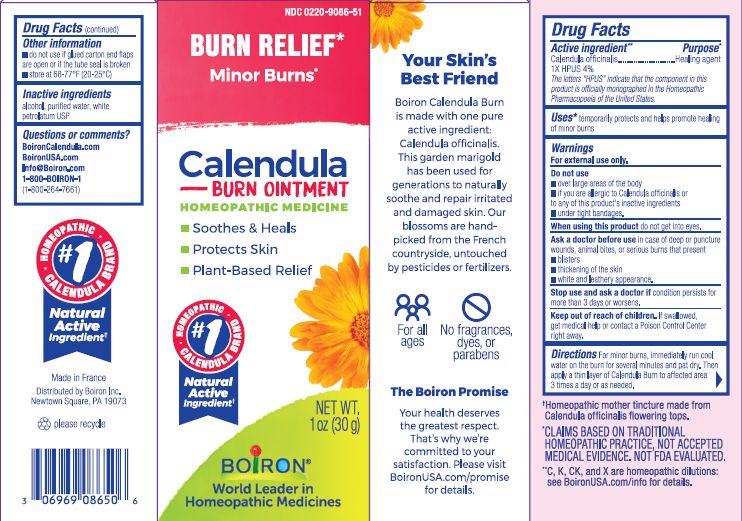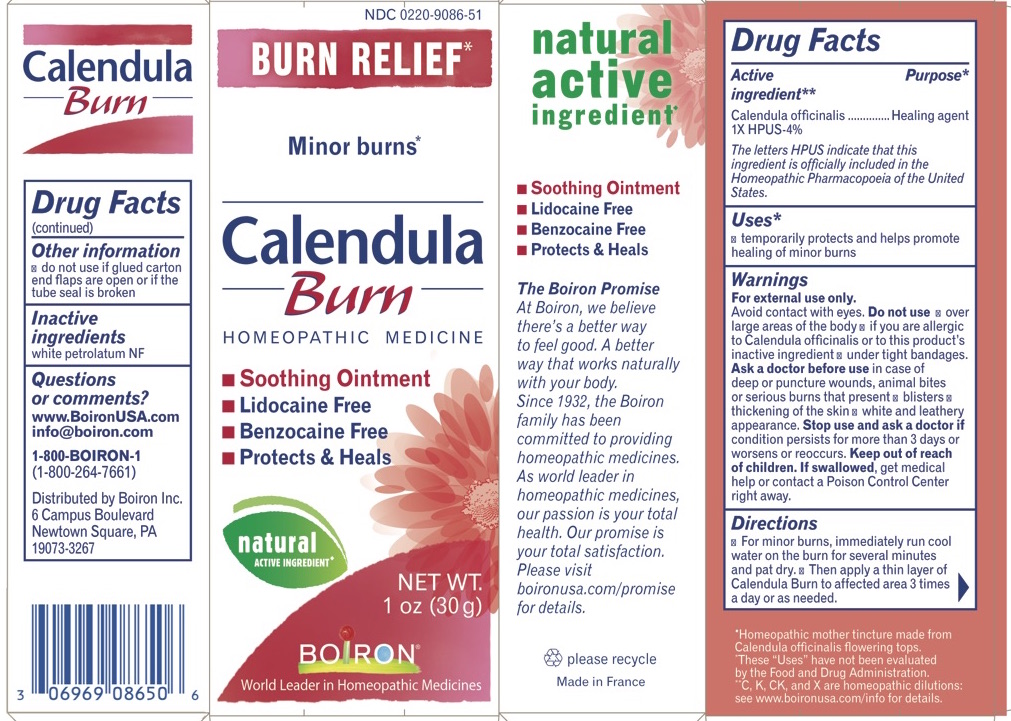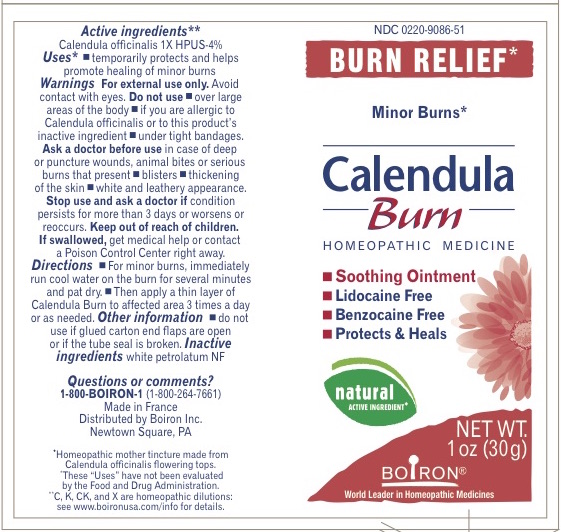 DRUG LABEL: CALENDULA
NDC: 0220-9086 | Form: OINTMENT
Manufacturer: Boiron
Category: homeopathic | Type: HUMAN OTC DRUG LABEL
Date: 20230220

ACTIVE INGREDIENTS: CALENDULA OFFICINALIS FLOWERING TOP 1 [hp_X]/1 g
INACTIVE INGREDIENTS: ALCOHOL; PETROLATUM; WATER

Calendula Burn

ACTIVE INGREDIENT

Calendula Officinalis 1X HPUS 4%

The letters "HPUS" indicate that the components in this product are officially monographed in the Homeopathic Pharmacopoeia of the United States.

INDICATIONS AND USAGE

- Temporarily protects and helps promote healing of minor burns.

Do not use

- Over large areas of the body
- If you are allergic to Calendula officinalis or to this product's inactive ingredients.
- Under tight bandages.
- Do not use if glued carton end flaps are broken or if the tube seal is broken.

DOSAGE AND ADMINISTRATION

For minor burns, immediately run cool water on the burn for several minutes and dry.

- Then apply a thin layer of Calendula Burn to affected area 3 times a day or as needed.

INACTIVE INGREDIENT

White petrolatum USP, alcohol, purfied water

HOW SUPPLIED

Tube 1 OZ (30 G)

PURPOSE

Calendula officinalis 1X HPUS 4%... Healing agent

STORAGE AND HANDLING

Store below 68-77° F (20-25° C)

Questions, Comments?

BoironCalendula.com

BoironUSA.com
info@boiron.com

1-800-BOIRON-1
(1-800-264-7661)

Distributed by Boiron Inc.
Newtown Square, PA 19073-3267

Ask a doctor before use in case of deep puncture wounds, animal bites or serious burns that present

- bisters
- thickening of the skin
- white and leathery appearance.

Stop use and ask a doctor if condition persists for more than 3 days or worsens or reoccurs.

Keep out of reach of children

Soothes & Heals

Protects Skin

Plant-based relief

No fragrances, dyes or parabens

For all ages

Burn Relief*

Minor Burns*

ɨ Homeopathic mother tincture made from Calendula officinalis flowering tops.

*CLAIMS BASED ON TRADITIONAL HOMEOPATHIC PRACTICE, NOT ACCEPTED MEDICAL EVIDENCE. NOT FDA EVALUATED.
*C,K,CK, and X are homeopathic dilutions: see BoironUSA.com/info for details.

WARNINGS

For external use only. Avoid contact with eyes.

If swallowed, get medical help or contact a Poison Control Center right away.